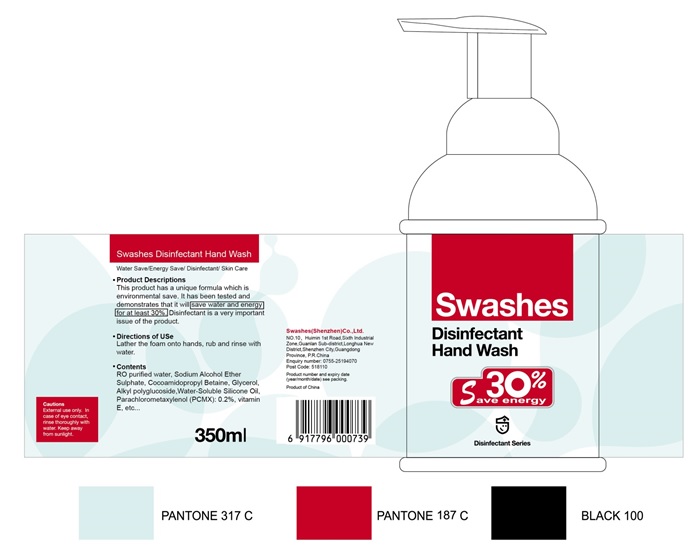 DRUG LABEL: Disinfectant Hand Wash
NDC: 74974-007 | Form: LIQUID
Manufacturer: Swashes (Shenzhen) Co., Ltd.
Category: otc | Type: HUMAN OTC DRUG LABEL
Date: 20200409

ACTIVE INGREDIENTS: CHLOROXYLENOL 0.22 g/100 mL
INACTIVE INGREDIENTS: DECYL GLUCOSIDE; EDETATE SODIUM; CITRIC ACID MONOHYDRATE; METHYLISOTHIAZOLINONE; .ALPHA.-TOCOPHEROL; GLYCERIN; METHYLCHLOROISOTHIAZOLINONE; FD&C BLUE NO. 1; SODIUM LAURETH-5 SULFATE; COCAMIDOPROPYL BETAINE; WATER

Disinfectant Hand Wash 74974-007

Disinfectant Hand Wash

Active Ingredient(s)

CHLOROXYLENOL 0.22g/100mL

Purpose: Antiseptic

Purpose

Antiseptic, Disinfectant Hand Wash

Use

Disinfectant Hand Wash to help reduce bacteria that potentially can cause disease. For use when soap and water are not available.

Warnings

For external use only. Flammable. Keep away from heat or flame

Do not use

- in children less than 2 months of age
- on open skin wounds

When using this product keep out of eyes, ears, and mouth. In case of contact with eyes, rinse eyes thoroughly with water.
Stop use and ask a doctor if irritation or rash occurs. These may be signs of a serious condition.
Keep out of reach of children. If swallowed, get medical help or contact a Poison Control Center right away.

Stop use and ask a doctor if irritation or rash occurs. These may be signs of a serious condition.

Keep out of reach of children. If swallowed, get medical help or contact a Poison Control Center right away.

Directions

- Place enough product on hands to cover all surfaces. Rub hands together until dry.
- Supervise children under 6 years of age when using this product to avoid swallowing.

Other information

- Store between 15-30C (59-86F)
- Avoid freezing and excessive heat above 40C (104F)

Inactive ingredients

SODIUM LAURETH-5 SULFATE
COCAMIDOPROPYL BETAINE
DECYL GLUCOSIDE
EDETATE SODIUM
CITRIC ACID MONOHYDRATE
Medicinal Glycerin
METHYLCHLOROISOTHIAZOLINONE
METHYLISOTHIAZOLINONE
Vitamin E
Brilliant Blue
Purity Water

Package Label - Principal Display Panel

350 mL NDC: 74974-007-01